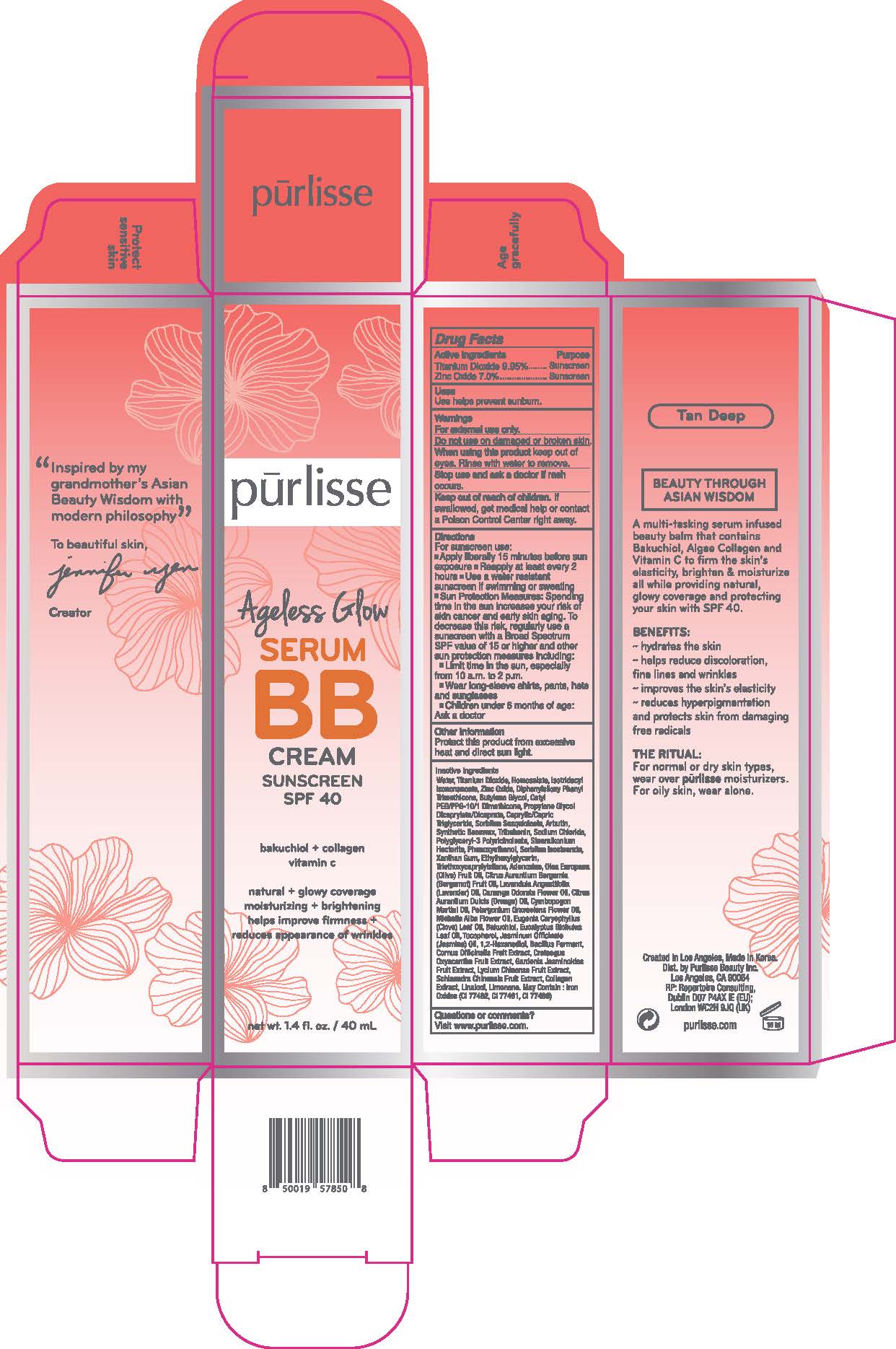 DRUG LABEL: Ageless Glow Serum BB Cream Sunscreen SPF 40 - Tan Deep
NDC: 72407-429 | Form: CREAM
Manufacturer: Pur-lisse Beauty, LLC
Category: otc | Type: HUMAN OTC DRUG LABEL
Date: 20251230

ACTIVE INGREDIENTS: HOMOSALATE 9.5 g/100 mL; ZINC OXIDE 7 g/100 mL; TITANIUM DIOXIDE 7.99 g/100 mL
INACTIVE INGREDIENTS: ISOTRIDECYL ISONONANOATE; DIPHENYLSILOXY PHENYL TRIMETHICONE; ARBUTIN; EUGENIA CARYOPHYLLUS (CLOVE) LEAF OIL; ADENOSINE; 1,2-HEXANEDIOL; POLYGLYCERYL-3 PENTARICINOLEATE; EUCALYPTUS GLOBULUS LEAF OIL; JASMINUM OFFICINALE FLOWER; CITRUS AURANTIUM BERGAMIA (BERGAMOT) FRUIT OIL; SCHISANDRA CHINENSIS FRUIT; CETYL PEG/PPG-10/1 DIMETHICONE (HLB 2); CORNUS OFFICINALIS FRUIT; BAKUCHIOL; BUTYLENE GLYCOL; OLEA EUROPAEA (OLIVE) FRUIT OIL; CANANGA ODORATA FLOWER OIL; MICHELIA ALBA FLOWER OIL; BACILLUS POLYFERMENTICUS; TRIBEHENIN; CAPRYLIC/CAPRIC TRIGLYCERIDE; LINALOOL, (+/-)-; WATER; LAVANDULA ANGUSTIFOLIA (LAVENDER) OIL; TOCOPHEROL; TRIETHOXYCAPRYLYLSILANE; SORBITAN ISOSTEARATE; SYNTHETIC BEESWAX; CITRUS AURANTIUM DULCIS (ORANGE) OIL; LYCIUM CHINENSE FRUIT; SORBITAN SESQUIOLEATE; CYMBOPOGON MARTINI OIL; CRATAEGUS LAEVIGATA FRUIT; PHENOXYETHANOL; XANTHAN GUM; SODIUM CHLORIDE; LIMONENE, (+)-; MARINE COLLAGEN, SOLUBLE; STEARALKONIUM HECTORITE; ETHYLHEXYLGLYCERIN; PROPYLENE GLYCOL DICAPRYLATE/DICAPRATE; PELARGONIUM GRAVEOLENS FLOWER OIL; GARDENIA JASMINOIDES FRUIT

Drug Facts

Active Ingredients

Homosalate 9.5%

Titanium Dioxide 7.99%

Zinc Oxide 7.0%

Purpose

Sunscreen

Uses

Use helps prevent sunburn.

Warnings

For external use only.

Do not use on damage or broken skin.

When using this product keep out of eyes. Rinse with water to remove.

Stop use and ask a doctor if rash occurs.

Keep out of reach of children. If swallowed, get medical help or contact a Poison Control Center right away.

Directions

For sunscreen use:

- Apply liberally 15 minutes before sun exposure
- Reapply at least every 2 hours
- Use a water resistant sunscreen if swimming or sweating
- Sun Protection Measures: Spending time in the sun increases your risk of skin cancer and early skin aging. To decrease this risk, regularly use a sunscreen with a Broad Spectrum SPF value of 15 or higher and other sun protection measures including:
- Limit time in the sun, especially from 10 a.m. to 2 p.m.
- Wear long-sleeve shirts, pants, hats and sunglasses
- Children under 6 months of age: Ask a doctor

Other Information

Protect this product from excessive heat and direct sun light.

Inactive Ingredients

Water, Isotridecyl Isononanoate, Diphenylsiloxy Phenyl Trimethicone, Butylene Glycol, Cetyl PEG/PPG-10/1 Dimethicone,Propylene Glycol Dicaprylate/Dicaprate, Caprylic/Capric Triglyceride, Sorbitan Sesquioleate, Synthetic Beeswax, Arbutin, Sodium Chloride, Tribehenin, Polyglyceryl-3 Polyricinoleate, Stearalkonium Hectorite, Phenoxyethanol, Sorbitan Isostearate, Xanthan Gum, Ethylhexylglycerin, Triethoxycaprylylsilane, Adenosine, Olea Europaea (Olive) Fruit Oil, Citrus Aurantium Bergamia (Bergamot) Fruit Oil, Lavandula Angustifolia (Lavender) Oil, Cananga Odorata Flower Oil, Citrus Aurantium Dulcis (Orange) Oil, Pelargonium Graveolens Flower Oil, Cymbopogon Martini Oil, Michelia Alba Flower Oil, Eugenia Caryophyllus (Clove) Leaf Oil, Bakuchiol, Eucalyptus Globulus Leaf Oil, Tocopherol, Jasminum Officinale (Jasmine) Oil, 1,2-Hexanediol, Bacillus Ferment, Cornus Officinalis Fruit Extract, Crataegus Oxyacantha Fruit Extract, Lycium Chinense Fruit Extract, Gardenia Jasminoides Fruit Extract, Schisandra Chinensis Fruit Extract, Collagen Extract, Linalool, Limonene. May Contain: Iron Oxides (CI 77492, CI 77491, CI 77499)

Questions or comments?

Visit www.purlisse.com.

Principal Display Panel - Ageless Glow Serum BB Cream Sunscreen SPF 40 - Tan Deep

pūrlisse

Ageless Glow

Serum

BB

CREAM

SUNSCREEN

SPF 40

bakuchiol + collagen

vitamin c

natural + glowy coverage

moisturizing + brightening

helps improve firmness +

reduces appearance of

wrinkles

1.4 fl. oz. / 40 mL